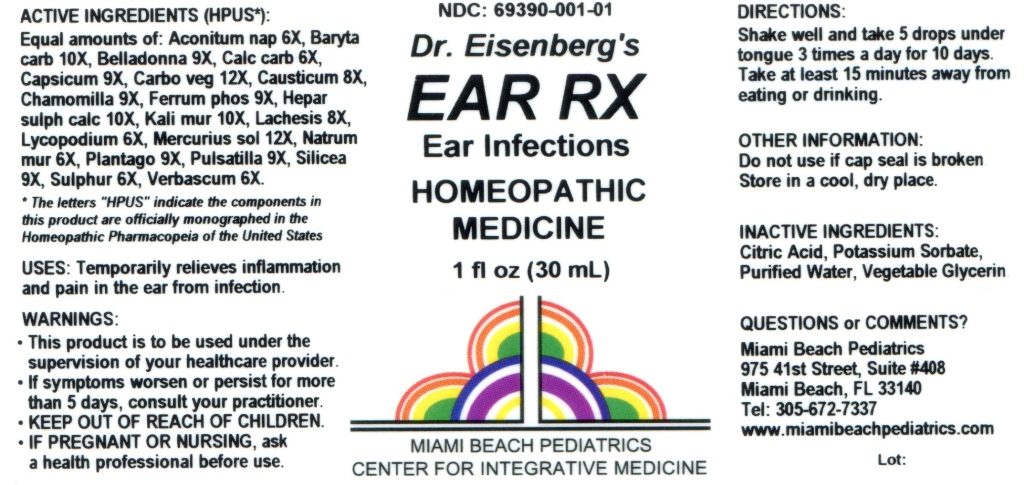 DRUG LABEL: EAR RX
NDC: 69390-001 | Form: LIQUID
Manufacturer: Miami Beach Pediatrics pa
Category: homeopathic | Type: HUMAN OTC DRUG LABEL
Date: 20211229

ACTIVE INGREDIENTS: ACONITUM NAPELLUS 6 [hp_X]/1 mL; BARIUM CARBONATE 10 [hp_X]/1 mL; ATROPA BELLADONNA 9 [hp_X]/1 mL; OYSTER SHELL CALCIUM CARBONATE, CRUDE 6 [hp_X]/1 mL; CAPSICUM 9 [hp_X]/1 mL; ACTIVATED CHARCOAL 12 [hp_X]/1 mL; CAUSTICUM 8 [hp_X]/1 mL; MATRICARIA RECUTITA 9 [hp_X]/1 mL; FERROSOFERRIC PHOSPHATE 9 [hp_X]/1 mL; CALCIUM SULFIDE 10 [hp_X]/1 mL; POTASSIUM CHLORIDE 10 [hp_X]/1 mL; LACHESIS MUTA VENOM 8 [hp_X]/1 mL; LYCOPODIUM CLAVATUM SPORE 6 [hp_X]/1 mL; MERCURIUS SOLUBILIS 12 [hp_X]/1 mL; SODIUM CHLORIDE 6 [hp_X]/1 mL; PLANTAGO MAJOR 9 [hp_X]/1 mL; PULSATILLA VULGARIS 9 [hp_X]/1 mL; SILICON DIOXIDE 9 [hp_X]/1 mL; SULFUR 6 [hp_X]/1 mL; VERBASCUM THAPSUS 6 [hp_X]/1 mL
INACTIVE INGREDIENTS: CITRIC ACID MONOHYDRATE; POTASSIUM SORBATE; WATER; GLYCERIN

Ear RX

ACTIVE INGREDIENTS (HPUS*):

Equal amounts of: Aconitum nap 6X, Baryta carb 10X, Belladonna 9X, Calc carb 6X, Capsicum 9X, Carbo veg 12X, Causticum 8X, Chamomilla 9X, Ferrum phos 9X, Hepar sulph calc 10X, Kali mur 10X, Lachesis 8X, Lycopodium 6X, Mercurius sol 12X, Natrum mur 6X, Plantago 9X, Pulsatilla 9X, Silicea 9X, Sulphur 6X, Verbascum 6X.

*The letters "HPUS" indicate the components in this product are officially monographed in the Homeopathic Pharmacopeia of the United States.

USES:

Temporarily relieves inflammation and pain in the ear from infection.

WARNINGS:

- This product is to be used under the supervision of your healthcare provider.
- If symptoms worsen or persist for more than 5 days, consult your practitioner.
- IF PREGNANT OR NURSING, ask a health professional before use.

- KEEP OUT OF THE REACH OF CHILDREN.

DIRECTIONS:

Shake well and take 5 drops under tongue 3 times a day for 10 days. Take at least 15 minutes away from eating or drinking.

OTHER INFORMATION:

Do not use if cap seal is broken. Store in a cool, dry place.

INACTIVE INGREDIENTS:

Citric Acid, Potassium Sorbate, Purified Water, Vegetable Glycerin.

QUESTIONS or COMMENTS?

Miami Beach Pediatrics

975 41st Street, Suite #408

Miami Beach, FL 33140

Tel: 305-672-7337

www.miamibeachpediatrics.com

PACKAGE LABEL

NDC: 69390-001-01

Dr. Eisenberg's

EAR RX

Ear Infections

HOMEOPATHIC MEDICINE

1 fl oz (30 mL)

MIAMI BEACH PEDIATRICS

CENTER FOR INTEGRATIVE MEDICINE

PURPOSE

Ear Infections